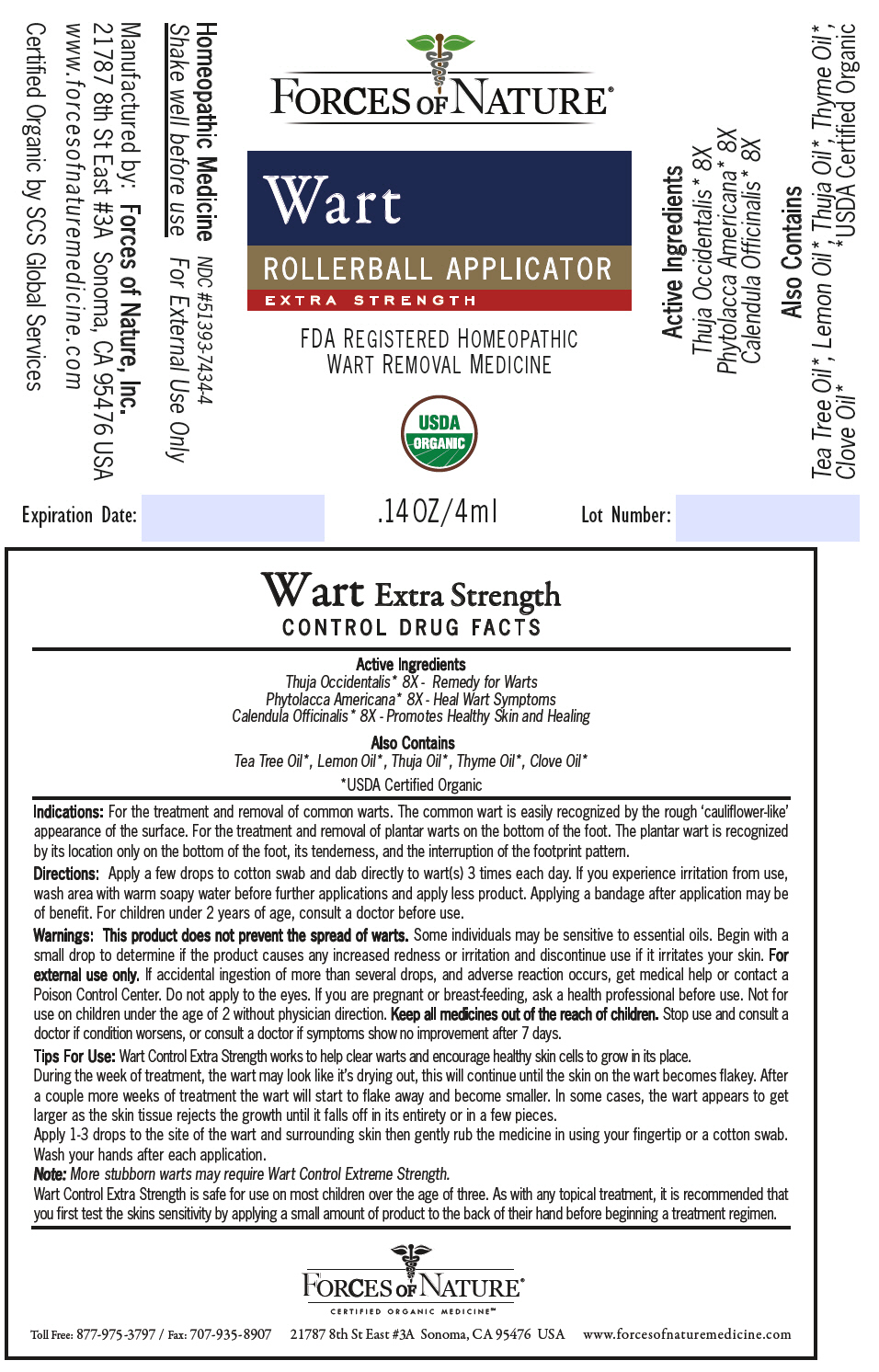 DRUG LABEL: Wart Control 
NDC: 51393-7434 | Form: SOLUTION/ DROPS
Manufacturer: Forces of Nature
Category: homeopathic | Type: HUMAN OTC DRUG LABEL
Date: 20200427

ACTIVE INGREDIENTS: CALENDULA OFFICINALIS FLOWERING TOP 8 [hp_X]/1000 mL; PHYTOLACCA AMERICANA ROOT 8 [hp_X]/1000 mL; THUJA OCCIDENTALIS LEAFY TWIG 8 [hp_X]/1000 mL
INACTIVE INGREDIENTS: CEDAR LEAF OIL; Lemon Oil; Tea Tree Oil; Clove Oil; Thyme Oil

Wart Control
Extra Strength

DRUG FACTS

Active Ingredients

Thuja Occidentalis [USDA Certified Organic] 8X - Remedy for Warts

Phytolacca Americana 8X - Heal Wart Symptoms

Calendula Officinalis 8X - Promotes Healthy Skin and Healing

Also Contains

Tea Tree Oil, Lemon Oil, Thuja Oil, Thyme Oil, Clove Oil

Indications

PURPOSE

For the treatment and removal of common warts. The common wart is easily recognized by the rough 'cauliflower-like' appearance of the surface. For the treatment and removal of plantar warts on the bottom of the foot. The plantar wart is recognized by its location only on the bottom of the foot, its tenderness, and the interruption of the footprint pattern.

Directions

Apply a few drops to cotton swab and dab directly to wart(s) 3 times each day. If you experience irritation from use, wash area with warm soapy water before further applications and apply less product. Applying a bandage after application may be of benefit. For children under 2 years of age, consult a doctor before use.

Warnings

This product does not prevent the spread of warts. Some individuals may be sensitive to essential oils. Begin with a small drop to determine if the product causes any increased redness or irritation and discontinue use if it irritates your skin. For external use only. If accidental ingestion of more than several drops, and adverse reaction occurs, get medical help or contact a Poison Control Center. Do not apply to the eyes. If you are pregnant or breast-feeding, ask a health professional before use. Not for use on children under the age of 2 without physician direction.

KEEP OUT OF REACH OF CHILDREN

Keep all medicines out of the reach of children. Stop use and consult a doctor if condition worsens, or consult a doctor if symptoms show no improvement after 7 days.

Tips For Use

Wart Control Extra Strength works to help clear warts and encourage healthy skin cells to grow in its place. During the week of treatment, the wart may look like it's drying out, this will continue until the skin on the wart becomes flakey. After a couple more weeks of treatment the wart will start to flake away and become smaller. In some cases, the wart appears to get larger as the skin tissue rejects the growth until it falls off in its entirety or in a few pieces.

Apply 1-3 drops to the site of the wart and surrounding skin then gently rub the medicine in using your fingertip or a cotton swab.

Wash your hands after each application.

Note: More stubborn warts may require Wart Control Extreme Strength.

Wart Control Extra Strength is safe for use on most children over the age of three. As with any topical treatment, it is recommended that you first test the skins sensitivity by applying a small amount of product to the back of their hand before beginning a treatment regimen.

Manufactured by: Forces of Nature, Inc.
21787 8th St East #3A Sonoma, CA 95476 USA

PRINCIPAL DISPLAY PANEL - 4 ml Bottle Label

FORCES OF NATURE ®

Wart
ROLLERBALL APPLICATOR
EXTRA STRENGTH

FDA REGISTERED HOMEOPATHIC
WART REMOVAL MEDICINE

USDA
ORGANIC

.14 OZ/4ml